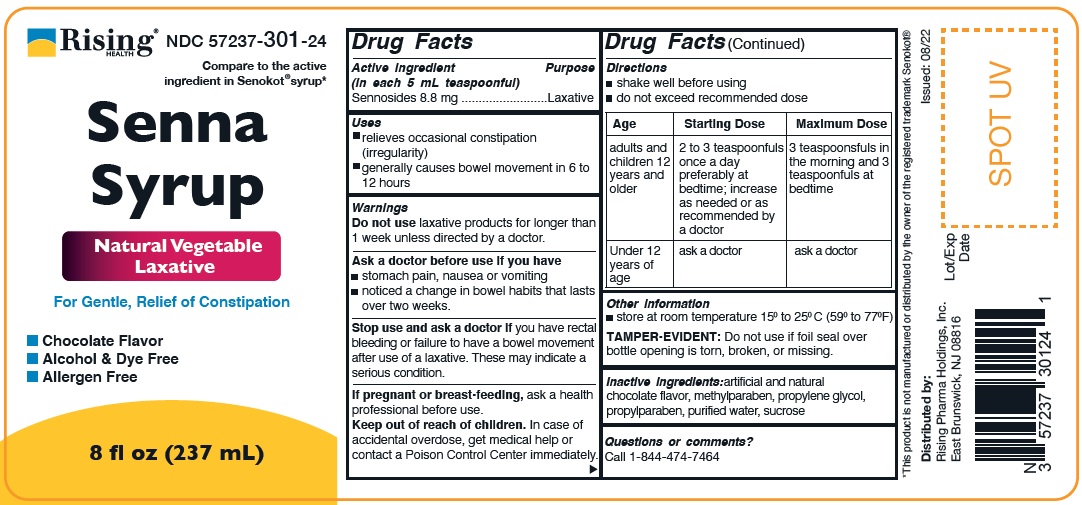 DRUG LABEL: Senna Syrup
NDC: 57237-301 | Form: LIQUID
Manufacturer: Rising Pharma Holdings, Inc.
Category: otc | Type: HUMAN OTC DRUG LABEL
Date: 20241018

ACTIVE INGREDIENTS: SENNOSIDES 8.8 mg/5 mL
INACTIVE INGREDIENTS: METHYLPARABEN; PROPYLENE GLYCOL; PROPYLPARABEN; WATER; SUCROSE

ACTIVE INGREDIENT

Senna Syrup

Active ingredient

(in each 5 mL teaspoonful)

Sennosides - 8.8 mg

Purpose

Laxative

Uses

- relieves occasional constipation (irregularity)
- generally causes bowel movement in 6 to 12 hours

Warnings

Do not use laxative products for longer than 1 week unless directed by a doctor.

Ask a doctor before use if you have

- stomach pain, nausea or vomitting
- noticed a change in bowel habits that lasts over two weeks.

Stope use and ask a doctor if you have rectal bleeding or failure to have a bowel movement after use of laxative. These may indicate a serious condition.

PREGNANCY

If pregnant or breast-feeding, ask a health professional before use.

Keep out of reach of children. In case of accidental overdose, get medical help or contact a Poison Control Center immediately.

Directions

- shake well before using
- Do not exceed recommended dose

Age | Starting Dose | Maximum Dose
adults and children 12 years and older | 2 to 3 teaspoonfuls once a day preferably at bedtime; increase as needed or as recommended by a doctor | 3 teaspoonfuls in the morning and 3 teaspoonfuls at bedtime
Under 12 years of age | ask a doctor | ask a doctor

Other information

- store at room temperature 15° to 25° C (59° to 77° F)

TAMPER-EVIDENT: Do not use if foil seal over bottle opening is torn, broken, or missing.

INACTIVE INGREDIENT

Inactive ingredients:artificial and natural chocolate flavor, methylparaben, propylene glycol, propylparaben, purified water, sucrose.

Questions or comments?

Call 1-844-474-7464